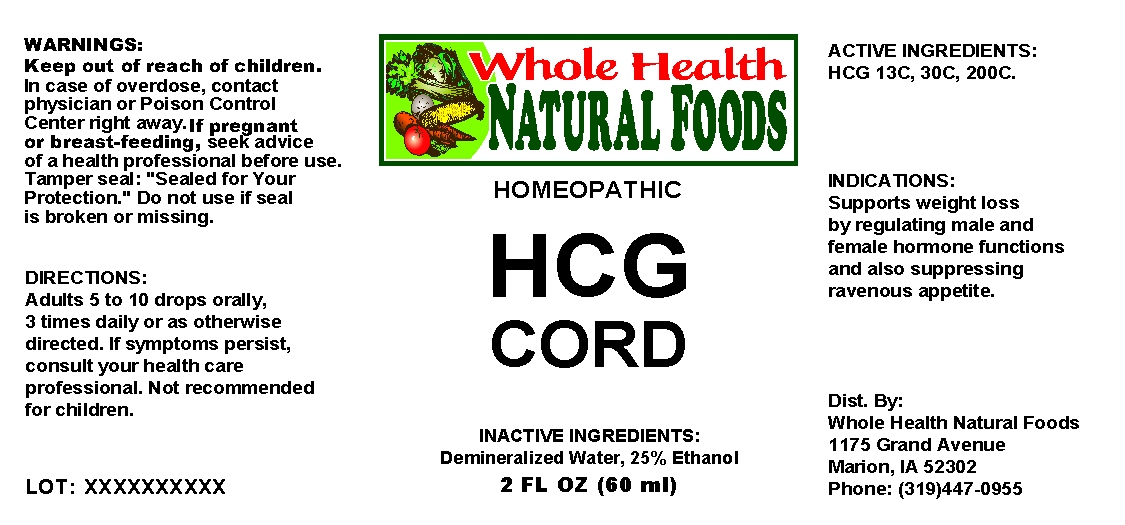 DRUG LABEL: HCG Cord
NDC: 57520-0340 | Form: LIQUID
Manufacturer: Apotheca Company
Category: homeopathic | Type: HUMAN OTC DRUG LABEL
Date: 20100430

ACTIVE INGREDIENTS: HUMAN CHORIONIC GONADOTROPIN 200 [hp_C]/1 mL
INACTIVE INGREDIENTS: WATER; ALCOHOL

HCG Cord

ACTIVE INGREDIENTS: HCG 13C, 30C, 200C.

PURPOSE

INDICATIONS: Supports weight loss by regulating male and female hormone functions and also suppressing ravenous appetite.

WARNINGS

WARNINGS: Keep out of reach of children. In case of overdose, contact physician or Poison Control Center right away.
If pregnant or breast-feeding, seek advice of a health professional before use.
Tamper seal. "Sealed for your protection." Do not use if seal is broken or missing.

DOSAGE AND ADMINISTRATION

DIRECTIONS: Adults 5 to 10 drops orally, 3 times daily or as otherwise directed. If symptoms persist, consult your health care professional. Not recommended for children.

INACTIVE INGREDIENTS: Demineralized water, 25% Ethanol

QUESTIONS

Dist. By:

Whole Health Natural Foods

1175 Grand Avenue

Marion, IA 52302

Phone: (319)-447-0955

PACKAGE LABEL

WHOLE HEALTH NATURAL FOODS

HOMEOPATHIC

HCG CORD

2 FL OZ (60 ML)